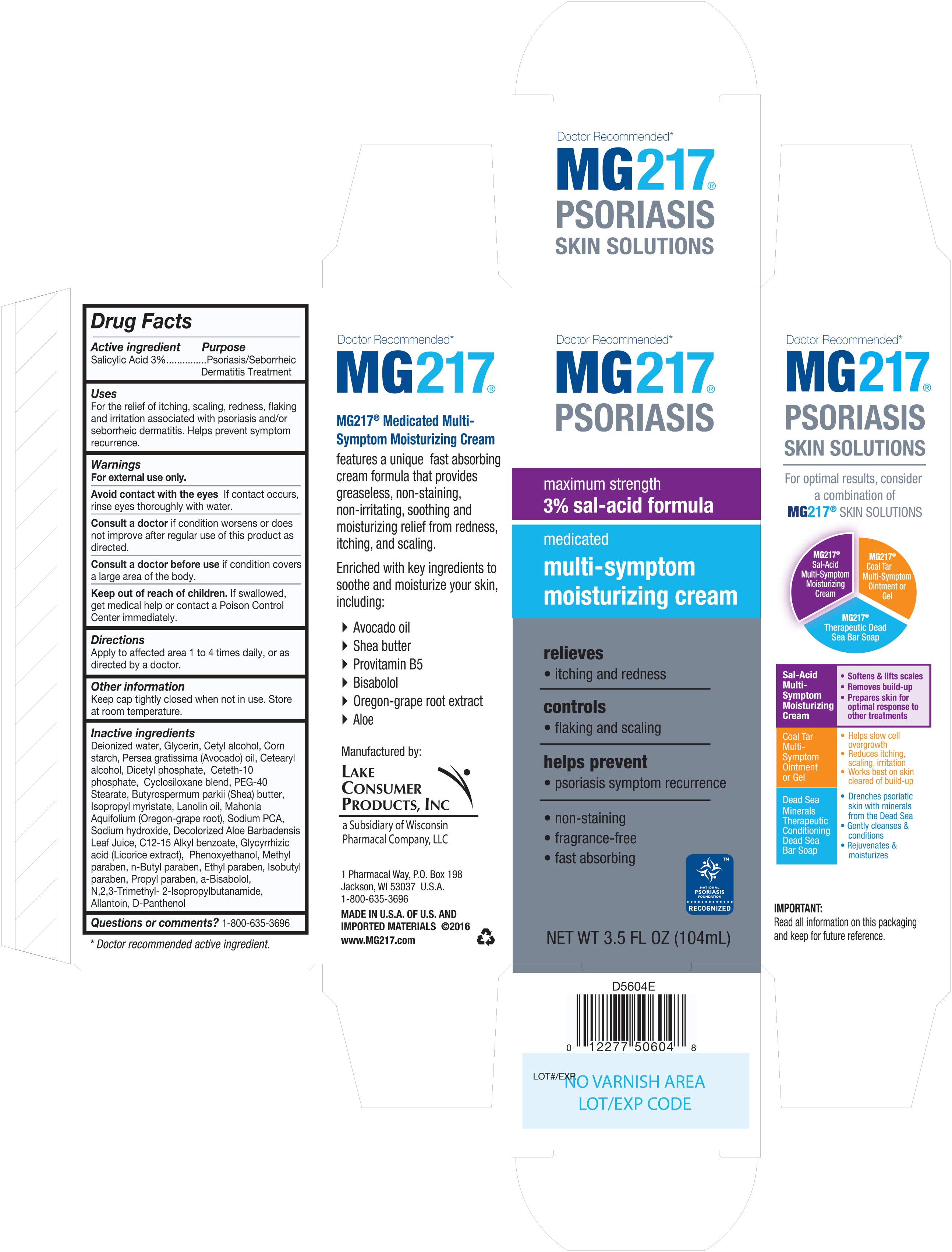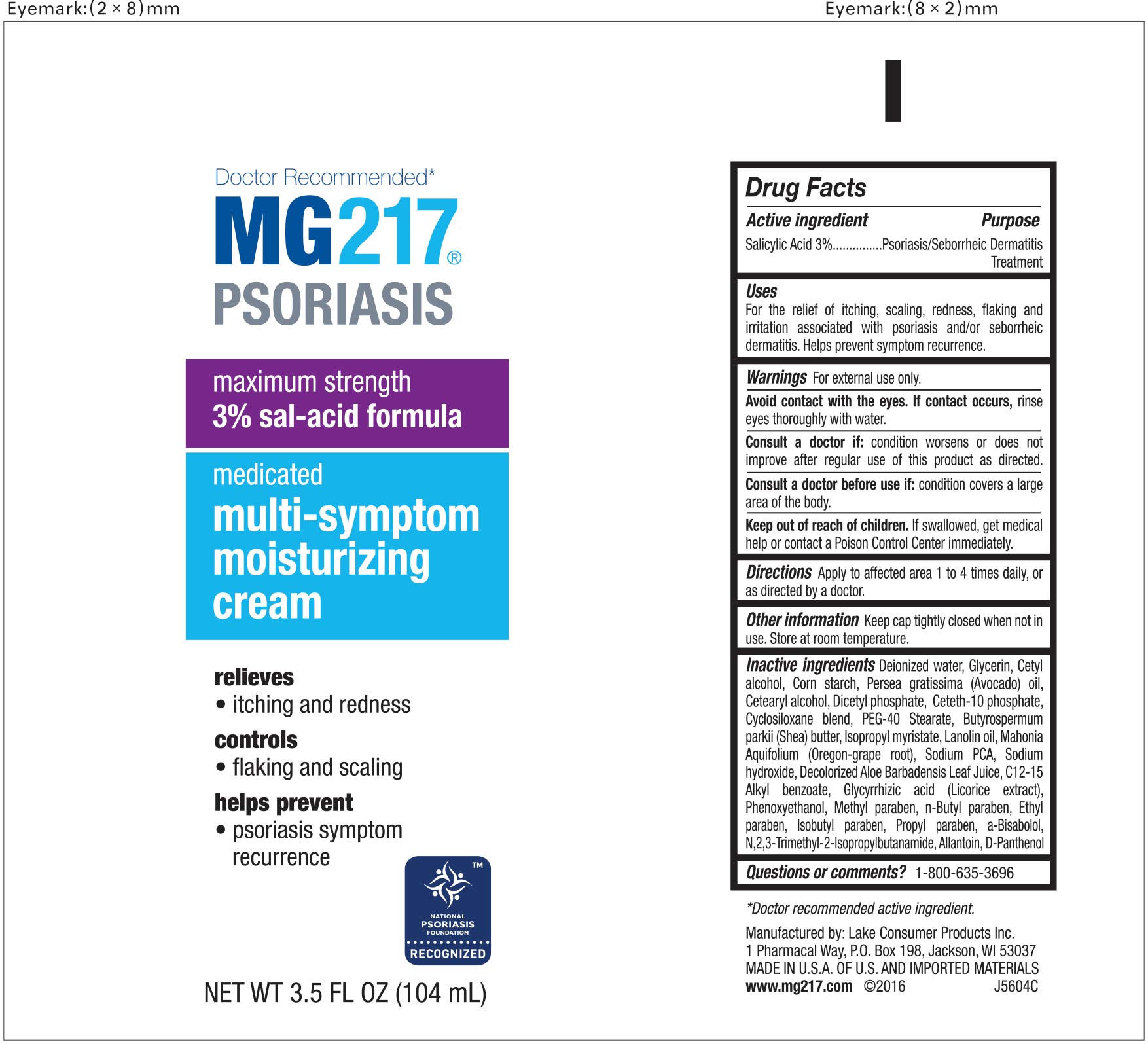 DRUG LABEL: MG217 Psoriasis
NDC: 68093-7203 | Form: SHAMPOO
Manufacturer: Wisconsin Pharmacal Company
Category: otc | Type: HUMAN OTC DRUG LABEL
Date: 20160303

ACTIVE INGREDIENTS: SALICYLIC ACID 0.03 g/1 g
INACTIVE INGREDIENTS: SHEA BUTTER; ALOE VERA LEAF; PEG-40 STEARATE; ALKYL (C12-15) BENZOATE; GLYCYRRHIZIN; PHENOXYETHANOL; ISOBUTYLPARABEN; PROPYLPARABEN; .ALPHA.-BISABOLOL, (+)-; ALLANTOIN, (+)-; DEXPANTHENOL; CETYL ALCOHOL; METHYL DIISOPROPYL PROPIONAMIDE; AVOCADO OIL; CETOSTEARYL ALCOHOL; CETETH-10 PHOSPHATE; CYCLOMETHICONE 6; CYCLOMETHICONE 5; ISOPROPYL MYRISTATE; LANOLIN OIL; MAHONIA AQUIFOLIUM ROOT; SODIUM PYRROLIDONE CARBOXYLATE; SODIUM HYDROXIDE; METHYLPARABEN; ETHYLPARABEN; WATER; GLYCERIN; STARCH, CORN; BUTYLPARABEN; DIHEXADECYL PHOSPHATE

Active Ingredient

Salicylic Acid 3%

Purpose

Psoriasis/Seborrheic Dermatitis Treatment

Uses

For the relief of itching, scaling, redness, flaking and irritation associated with psoriasis and/or seborrheic dermatitis. Helps prevents symptom recurrence.

Keep out of reach of children

If swallowed, get medical help or contact a Poison Control Center immediately.

Warnings

For external use only.

Avoid contact with the eyes If contact occurs, rinse eyes thoroughly with water.

Consult a doctor

if condition worsens or does not improve after regular use of this product as directed.

Consult a doctor before use if condition covers a large area of the body.

Other information

Keep cap tightly closed when not in use. Store at room temperature.

Questions or comments?

1-800-635-3696

Directions

Apply to affected area 1 to 4 times daily, or as directed by a doctor.

Inactive ingredients

Deionized water, Glycerin, Cetyl alcohol, Corn starch, Persea gratissima (Avocado) oil, Cetearyl alcohol, Dicetyl phosphate, Ceteth-10 phophate, Cyclosiloxane blend, PEG-40 Stearate, Butyrospermum parkii (Shea) butter, Isopropyl myristate, Lanolin oil, Mahonia Aquifolium (Oregon-grape root), Sodium PCA, Sodium hydroxide, Aloe vera, C12-15 Alkyl benzoate, Glycyrrhizic acid (Licorice extract), Phenoxyethanol, Methyl paraben, n-Butyl paraben, Ethyl paraben, Isobutyl paraben, Propyl paraben, a-Bisabolol, N,2,3-Trimethyl-2-Isopropylbutamide, Allantoin, D-Panthenol